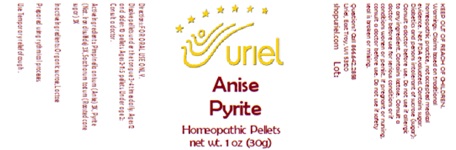 DRUG LABEL: Anise Pyrite
NDC: 48951-1036 | Form: PELLET
Manufacturer: Uriel Pharmacy Inc.
Category: homeopathic | Type: HUMAN OTC DRUG LABEL
Date: 20250122

ACTIVE INGREDIENTS: ANISE 3 [hp_X]/1 1; FERROUS DISULFIDE 3 [hp_X]/1 1; SUCROSE 3 [hp_X]/1 1
INACTIVE INGREDIENTS: LACTOSE

Anise Pyrite

INDICATIONS AND USAGE

Directions: FOR ORAL USE ONLY.

DOSAGE AND ADMINISTRATION

Dissolve pellets under the tongue 3-4 times daily. Ages 12 and older: 10 pellets. Ages 2-11: 5 pellets. Under age 2: Consult a doctor.

ACTIVE INGREDIENT

Active Ingredients: Pimpinella anisum (Anise) 3X, Pyrite (Nat. Iron disulfide) 3X, Saccharum tostum (Roasted cane sugar) 3X

Inactive Ingredients: Organic sucrose, Lactose

Prepared using rhythmical processes.

PURPOSE

Use: Temporary relief of cough.

KEEP OUT OF REACH OF CHILDREN.

WARNINGS

Warnings: Claims based on traditional homeopathic practice, not accepted medical evidence. Not FDA evaluated. Contains sugar. Diabetics and persons intolerant of sucrose (sugar): Consult a doctor before use. Do not use if allergic to any ingredient. Contains lactose. Consult a doctor before use for serious conditions or if conditions worsen or persist. If pregnant or nursing, consult a doctor before use. Do not use if safety seal is broken or missing.

QUESTIONS

Questions? Call 866.642.2858 Uriel, East Troy WI 53120 shopuriel.com Lot: